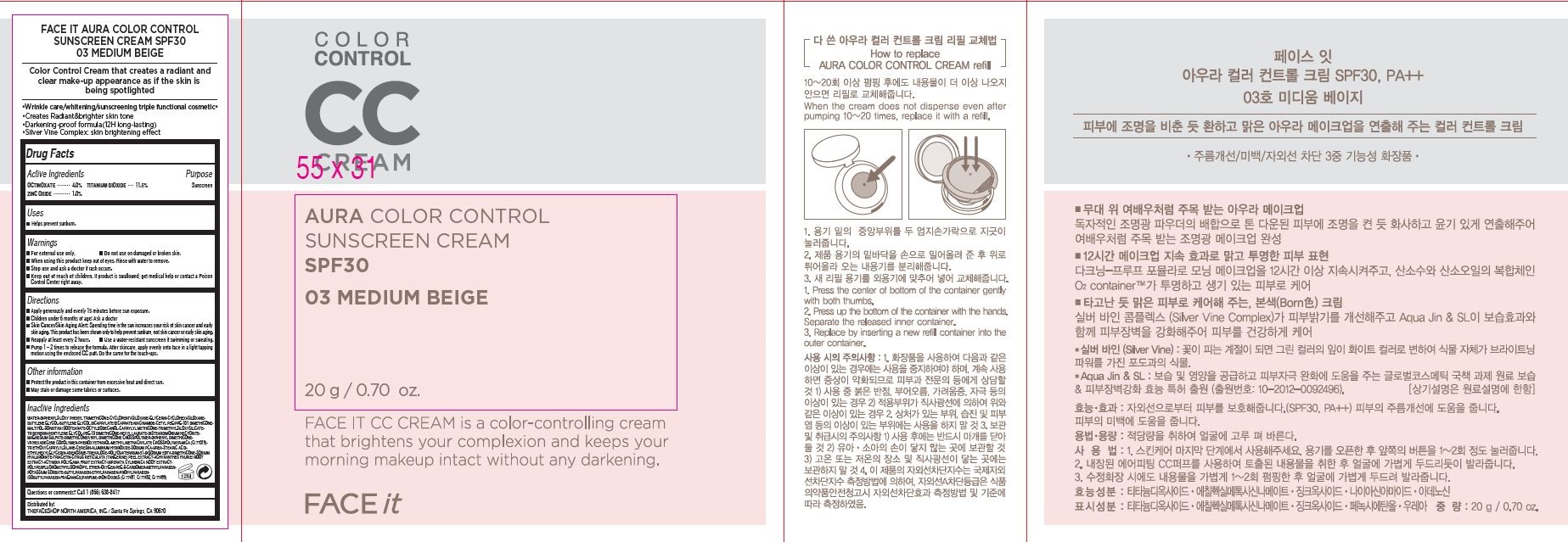 DRUG LABEL: FACE IT AURA COLOR CONTROL
NDC: 51523-675 | Form: CREAM
Manufacturer: THEFACESHOP CO., LTD.
Category: otc | Type: HUMAN OTC DRUG LABEL
Date: 20141120

ACTIVE INGREDIENTS: TITANIUM DIOXIDE 2.3 g/20 g; ZINC OXIDE .2 g/20 g; OCTINOXATE .8 g/20 g
INACTIVE INGREDIENTS: WATER

Active Ingredients

OCTINOXATE.............. 4.0%

TITANIUM DIOXIDE. 11.5%
ZINC OXIDE................. 1.0%

Purpose

Sunscreen

Sunscreen

Sunscreen

Warnings

For external use only.

Do not use on damaged or broken skin

When using this product keep out of eyes. Rinse with water to remove.

Stop use and ask a doctor if rash occurs.

Keep out of reach of children.

If product is swallowed, get medical help or contact a Poison Control Center right away.

Directions

Apply generously and evenly 15 minutes before sun exposure.
Children under 6 months of age: Ask a doctor
Skin Cancer/Skin Aging Alert: Spending time in the sun increases your risk of skin cancer and early skin. aging. This product has been shown only to help prevent sunburn, not skin cancer or early skin aging.
Reapply at least every 2 hours
Use a water-resistant sunscreen if swimming or sweating.

1. Pump 1 – 2 times to release the formula.

2. After skin care, apply evenly onto face in a light tapping motion using the enclosed CC puff.

3. Do the same for the touch-ups

Other Information

Protect the product in this container from excessive heat and direct sun

May stain or damage some fabrics or surfaces

Inactive Ingredients

WATER•DIPHENYLSILOXY PHENYL TRIMETHICONE•CYCLOPENTASILOXANE•GLYCERIN•CYCLOHEXASILOXANE•
BUTYLENE GLYCOL•BUTYLENE GLYCOL DICAPRYLATE/DICAPRATE•NIACINAMIDE•CETYL PEG/PPG-10/1 DIMETHICONE•
MALTITOL•SORBITAN ISOSTEARATE•OCTYLDODECANOL•CAPRYLYL METHICONE•TRIMETHYLSILOXYSILICATE•
TRIBEHENIN•PENTYLENE GLYCOL•PEG-10 DIMETHICONE•HEXYL LAURATE•DISTEARDIMONIUM HECTORITE•
MAGNESIUM SULFATE•DIMETHICONE/VINYL DIMETHICONE CROSSPOLYMER•DIPHENYL DIMETHICONE•
VP/HEXADECENE COPOLYMER•PHENOXYETHANOL•METHYL METHACRYLATE CROSSPOLYMER•MICA (CI 77019)•
TRIETHOXYCAPRYLYLSILANE•CERESIN•ALUMINUM HYDROXIDE•SODIUM PCA•UREA•STEARIC ACID•
ETHYLHEXYLGLYCERIN•ADENOSINE•TREHALOSE•POLYQUATERNIUM-51•DISODIUM EDTA•DIMETHICONE•SODIUM
HYALURONATE•TRIACETIN•CITRUS RETICULATA (TANGERINE) PEEL EXTRACT•ACHYRANTHES FAURIEI ROOT
EXTRACT•ACTINIDIA POLYGAMA FRUIT EXTRACT•IMPERATA CYLINDRICA ROOT EXTRACT•
POLYPERFLUOROMETHYLISOPROPYL ETHER•OXYGEN•PEG-8•CARBOMER•METHYLPARABEN•
POTASSIUM SORBATE•BUTYLPARABEN•ETHYLPARABEN•PROPYLPARABEN•
ISOBUTYLPARABEN•FRAGRANCE(PARFUM)•IRON OXIDES (CI 77491, CI 77492, CI 77499)

Questions or comments? Call 1 (866) 638-8417

Distributed by:

THEFACESHOP NORTH AMERICA, INC. / Santa Fe Springs, CA 90670

PACKAGE LABEL

COLOR CONTROLCC CREAM
AURA COLOR CONTROL
SUNSCREEN CREAM
SPF30
03 MEDIUM BEIGE

FACE IT CC CREAM is a color-controlling cream that brightens your complexion
and keeps your morning makeup intact without any darkening.

FACE it